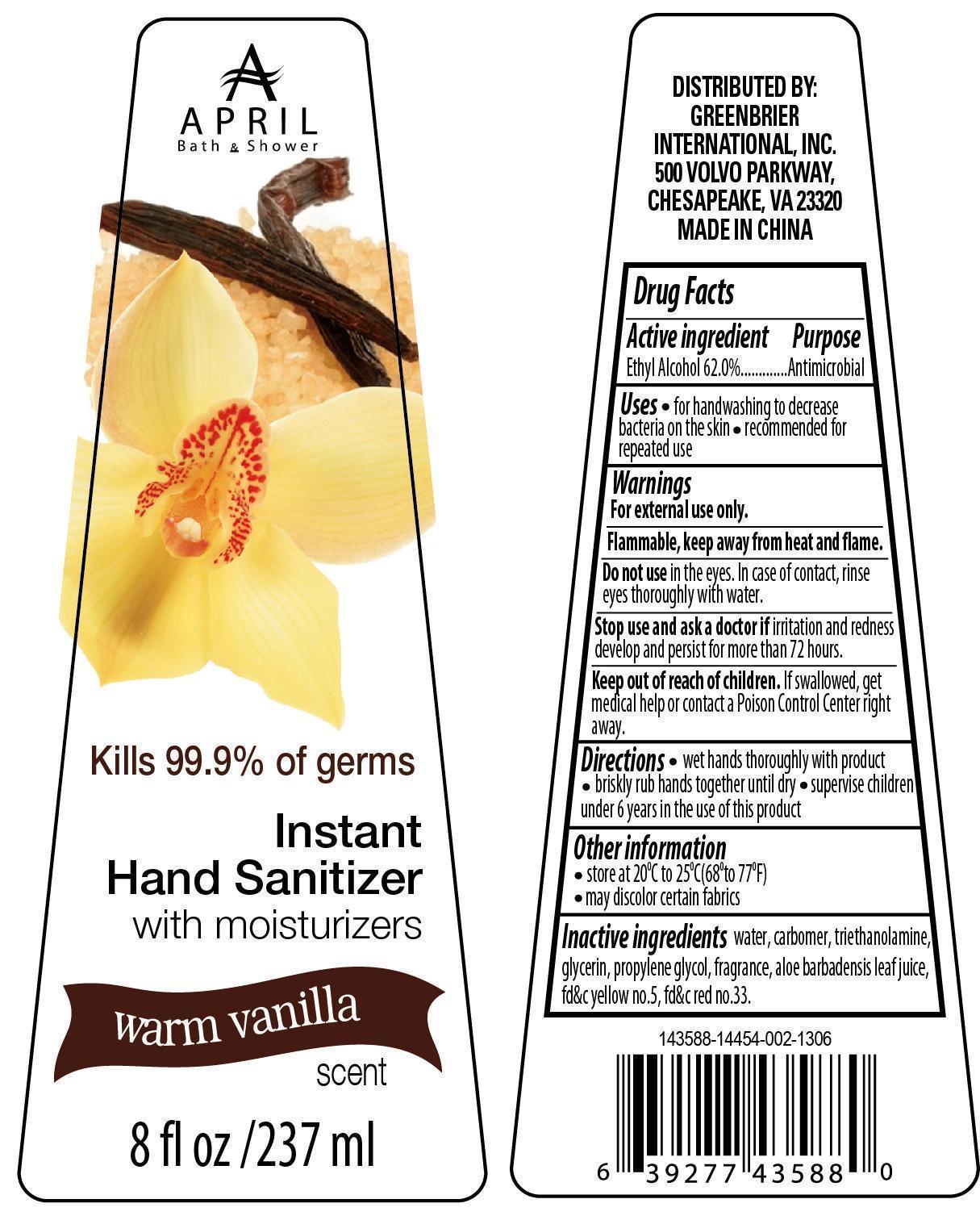 DRUG LABEL: Warm Vanilla Hand Sanitizer
NDC: 58503-004 | Form: GEL
Manufacturer: China Ningbo Shangge Cosmetic Technology Corp.
Category: otc | Type: HUMAN OTC DRUG LABEL
Date: 20221117

ACTIVE INGREDIENTS: ALCOHOL 147 mL/237 mL
INACTIVE INGREDIENTS: WATER; CARBOMER HOMOPOLYMER TYPE C (ALLYL PENTAERYTHRITOL CROSSLINKED); TROLAMINE; GLYCERIN; PROPYLENE GLYCOL; ALOE VERA LEAF; D&C RED NO. 33; FD&C YELLOW NO. 5

Warm Vanilla Hand Sanitizer

Active Ingredient Purpose

Ethyl Alcohol 62.0%...........................Antimicrobial

Uses

- for handwashing to decrease the bacteria on the skin
- recommended for repeated use

Keep out of reach of children. If swallowed, get medical help or contact a Poison Control Center right away.

Other information

- store at 20oC to 25oC (68o to 77oF)
- may discolor certain fabrics

Warnings

For external use only.

Flammable, keep away from heat and flame.

Do not use in the eyes. In case of contact, rinse eyes thoroughly with water.

Stop use and ask a doctor if irritation and redness develop and persist for more than 72 hours.

Directions

- wet hands thoroughly with product
- briskly rub hands together until dry
- supervise children under 6 years in the use of this product

Inactive Ingredients

water, carbomer, triethanolamine, glycerin, propylene glycol, fragrance, aloe barbadensis leaf juice, fd&c yellow no.5, fd&c red no.33.